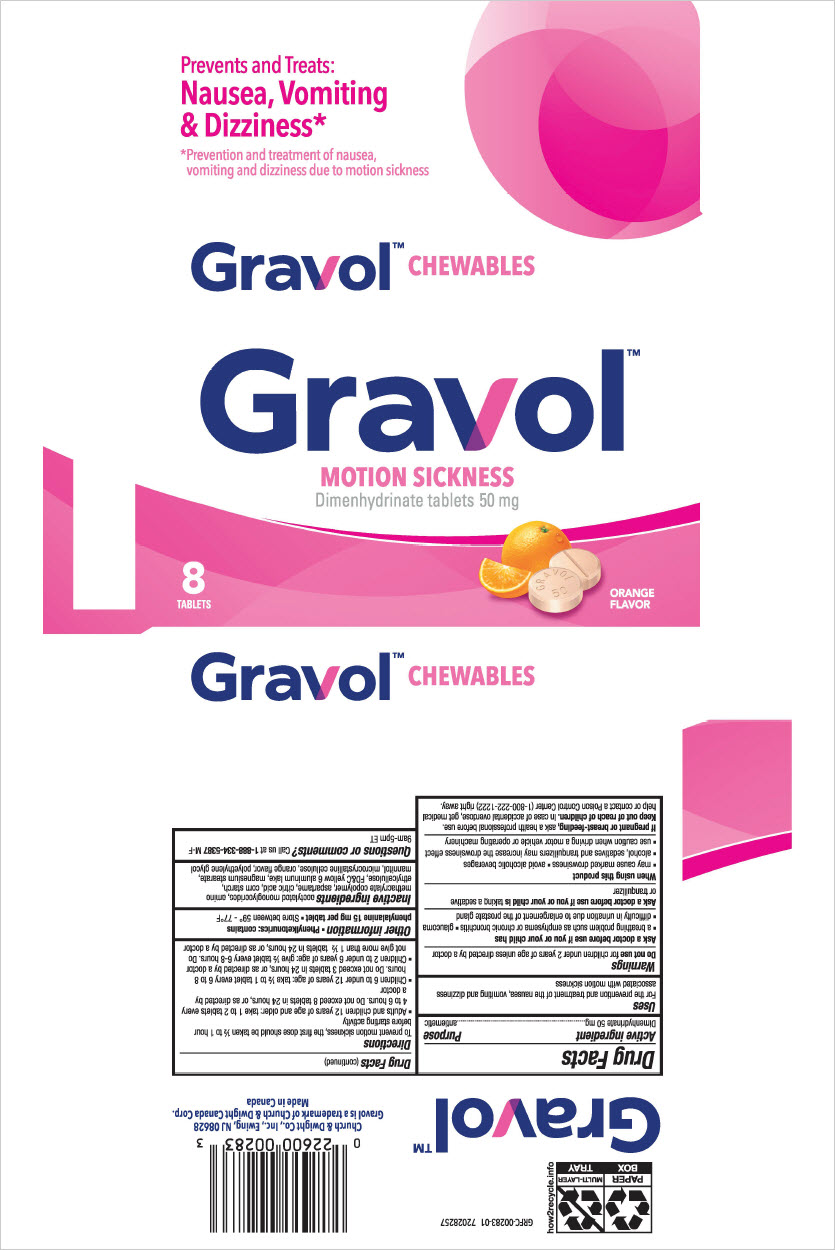 DRUG LABEL: Gravol Chewables Motion Sickness Dimenhydrinate
NDC: 10237-943 | Form: TABLET, CHEWABLE
Manufacturer: Church & Dwight Co., Inc.
Category: otc | Type: HUMAN OTC DRUG LABEL
Date: 20240301

ACTIVE INGREDIENTS: DIMENHYDRINATE 50 mg/1 1
INACTIVE INGREDIENTS: DIACETYLATED MONOGLYCERIDES; DIMETHYLAMINOETHYL METHACRYLATE - BUTYL METHACRYLATE - METHYL METHACRYLATE COPOLYMER; ASPARTAME; CITRIC ACID MONOHYDRATE; STARCH, CORN; ETHYLCELLULOSE (10 MPA.S); FD&C YELLOW NO. 6; MAGNESIUM STEARATE; MANNITOL; MICROCRYSTALLINE CELLULOSE; POLYETHYLENE GLYCOL, UNSPECIFIED

Gravol™ Chewables Motion Sickness Dimenhydrinate

Drug Facts

Active ingredient

Dimenhydrinate 50 mg

Purpose

antiemetic

Uses

For the prevention and treatment of the nausea, vomiting and dizziness associated with motion sickness

Warnings

Do not use for children under 2 years of age unless directed by a doctor

Ask a doctor before use if you or your child has

- a breathing problem such as emphysema or chronic bronchitis
- glaucoma
- difficulty in urination due to enlargement of the prostate gland

Ask a doctor before use if you or your child is taking a sedative or tranquilizer

When using this product

- may cause marked drowsiness
- avoid alcoholic beverages
- alcohol, sedatives and tranquilizers may increase the drowsiness effect
- use caution when driving a motor vehicle or operating machinery

PREGNANCY OR BREAST FEEDING

If pregnant or breast-feeding, ask a health professional before use.

Keep out of reach of children. In case of accidental overdose, get medical help or contact a Poison control Center (1-800-222-1222) right away.

Directions

To prevent motion sickness, the first dose should be taken ½ to 1 hour before starting activity

- Adults and children 12 years of age and older: take 1 to 2 tablets every 4 to 6 hours. Do not exceed 8 tablets in 24 hours, or as directed by a doctor
- Children 6 to under 12 years of age: take ½ to 1 tablet every 6 to 8 hours. Do not exceed 3 tablets in 24 hours, or as directed by a doctor
- Children 2 to under 6 years of age: give ½ tablet every 6-8 hours. Do not give more than 1 ½ tablets in 24 hours, or as directed by a doctor

Other information

- Phenylketunurics: contains phenylalanine 15 mg per tablet
- Store between 59° - 77°F

Inactive ingredients

acetylated monoglycendes, amino methacrylate copolymer, aspartame, citric acid, com starch, ethylcellulose, FD&C yellow 6 aluminum lake, magnesium stearate, mannitol, microcrystalline cellulose, orange flavor, polyethylene glycol

Questions or comments?

Call us at 1-888-334--5387 M-F 9am-5pm ET

PRINCIPAL DISPLAY PANEL - 50 mg Blister Pack Carton

Prevents and Treats:
Nausea, Vomiting
& Dizziness*

*Prevention and treatment of nausea,
vomiting and dizziness due to motion sickness

Gravol™ CHEWABLES

Gravol™
MOTION SICKNESS
Dimenhydrinate tablets 50 mg

8
TABLETS

ORANGE
FLAVOR